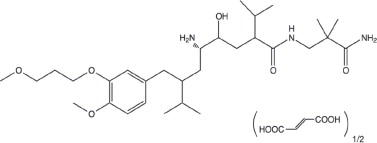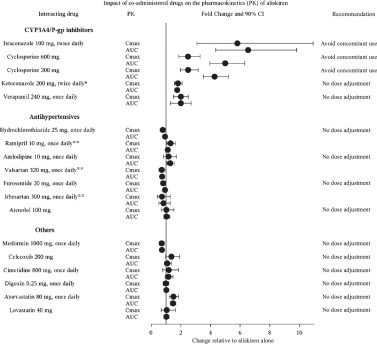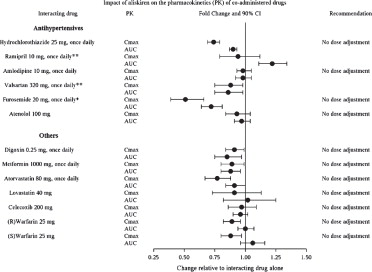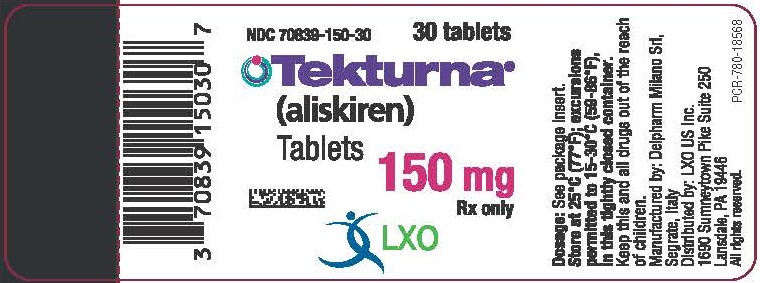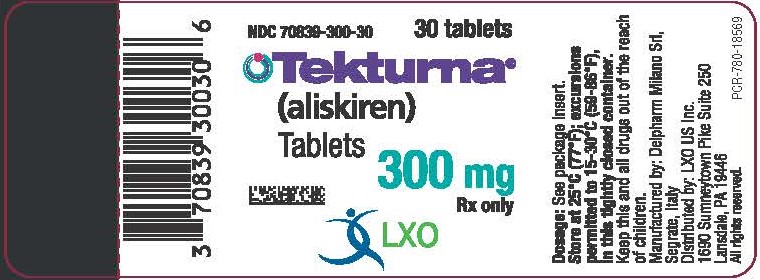 DRUG LABEL: Tekturna
NDC: 70839-150 | Form: TABLET, FILM COATED
Manufacturer: LXO US Inc.
Category: prescription | Type: HUMAN PRESCRIPTION DRUG LABEL
Date: 20240307

ACTIVE INGREDIENTS: ALISKIREN HEMIFUMARATE 150 mg/1 1
INACTIVE INGREDIENTS: SILICON DIOXIDE; CROSPOVIDONE; HYPROMELLOSES; FERRIC OXIDE RED; MAGNESIUM STEARATE; CELLULOSE, MICROCRYSTALLINE; POLYETHYLENE GLYCOL, UNSPECIFIED; TALC; TITANIUM DIOXIDE; FERROSOFERRIC OXIDE

HIGHLIGHTS OF PRESCRIBING INFORMATION

These highlights do not include all the information needed to use TEKTURNA safely and effectively. See full prescribing information for TEKTURNA.
TEKTURNA® (aliskiren) tablets, for oral use
Initial U.S. Approval: 2007

WARNING: FETAL TOXICITY

See full prescribing information for complete boxed warning.

- When pregnancy is detected, discontinue Tekturna as soon as possible. (5.1, 8.1)
- Drugs that act directly on the renin-angiotensin system can cause injury and death to the developing fetus. (5.1, 8.1)

1 INDICATIONS AND USAGE

Tekturna is a renin inhibitor (RI) indicated for the treatment of hypertension in adults and in pediatric patients weighing 50 kg or greater who are at least 6 years of age, to lower blood pressure. Lowering blood pressure reduces the risk of fatal and nonfatal cardiovascular events, primarily strokes and myocardial infarctions. (1.1)

2 DOSAGE AND ADMINISTRATION

- Starting dose (adults and pediatric patients): 150 mg once daily with a routine pattern with regard to meals. If blood pressure remains uncontrolled titrate up to 300 mg daily. (2.1)
- Majority of effect of given dose attained in 2 weeks. (2.1)

3 DOSAGE FORMS AND STRENGTHS

Tablets: 150 mg, 300 mg (3)

4 CONTRAINDICATIONS

Do not use with angiotensin receptor blockers (ARBs) or angiotensin- converting enzyme inhibitors (ACEIs) in patients with diabetes. (4)

Hypersensitivity to any of the components. (4)

Tekturna is contraindicated in pediatric patients less than 2 years of age. (4)

5 WARNINGS AND PRECAUTIONS

- Avoid concomitant use with ARBs or ACEIs particularly in patients with renal impairment [creatinine clearance (CrCl) <60 mL/min]. (5.2, 5.4)
- Anaphylactic Reactions and Head and Neck Angioedema. (5.3)
- Hypotension: Correct imbalances in volume and/or salt depleted patients. (5.4)
- Impaired Renal Function: Monitor serum creatinine periodically. (5.5)
- Hyperkalemia: Monitor potassium levels periodically. (5.6)

7 DRUG INTERACTIONS

- Cyclosporine or Itraconazole: Avoid concomitant use. (5.7, 7, 12.3)
- Nonsteroidal Anti-Inflammatory Drugs (NSAIDs): Increased risk of renal impairment and loss of antihypertensive effect. (7)

6 ADVERSE REACTIONS

Most common adverse reaction: diarrhea (incidence 2.3%) (6.1)

To report SUSPECTED ADVERSE REACTIONS, contact LXO US Inc. at 1-844-800-8007 or FDA at 1-800-FDA-1088 or www.fda.gov/medwatch.

8 USE IN SPECIFIC POPULATIONS

Lactation: Breastfeeding not recommended. (8.2)

FULL PRESCRIBING INFORMATION

WARNING: FETAL TOXICITY

When pregnancy is detected, discontinue Tekturna as soon as possible. (5.1, 8.1)

Drugs that act directly on the renin-angiotensin system can cause injury and death to the developing fetus. (5.1, 8.1)

1 INDICATIONS AND USAGE

1.1 Hypertension

Tekturna is indicated for the treatment of hypertension in adults and in pediatric patients weighing 50 kg or greater who are at least 6 years of age and older to lower blood pressure.

Lowering blood pressure reduces the risk of fatal and nonfatal cardiovascular events, primarily strokes and myocardial infarctions. These benefits have been seen in controlled trials of antihypertensive drugs from a wide variety of pharmacologic classes. There are no controlled trials demonstrating risk reduction with Tekturna.

Control of high blood pressure should be part of comprehensive cardiovascular risk management, including, as appropriate, lipid control, diabetes management, antithrombotic therapy, smoking cessation, exercise, and limited sodium intake. Many patients will require more than 1 drug to achieve blood pressure goals. For specific advice on goals and management, see published guidelines, such as those of the National High Blood Pressure Education Program's Joint National Committee on Prevention, Detection, Evaluation, and Treatment of High Blood Pressure (JNC).

Numerous antihypertensive drugs, from a variety of pharmacologic classes and with different mechanisms of action, have been shown in randomized controlled trials to reduce cardiovascular morbidity and mortality, and it can be concluded that it is blood pressure reduction, and not some other pharmacologic property of the drugs, that is largely responsible for those benefits. The largest and most consistent cardiovascular outcome benefit has been a reduction in the risk of stroke, but reductions in myocardial infarction and cardiovascular mortality have also been seen regularly.

Elevated systolic or diastolic pressure causes increased cardiovascular risk, and the absolute risk increase per mmHg is greater at higher blood pressures, so that even modest reductions of severe hypertension can provide substantial benefit. Relative risk reduction from blood pressure reduction is similar across populations with varying absolute risk, so the absolute benefit is greater in patients who are at higher risk independent of their hypertension (e.g., patients with diabetes or hyperlipidemia), and such patients would be expected to benefit from more aggressive treatment to a lower blood pressure goal.

Some antihypertensive drugs have smaller blood pressure effects (as monotherapy) in black patients, and many antihypertensive drugs have additional approved indications and effects (e.g., on angina, heart failure, or diabetic kidney disease). These considerations may guide selection of therapy.

2 DOSAGE AND ADMINISTRATION

2.1 Recommended Dosage

In adult patients and in pediatric patients weighing 50 kg or greater who are at least 6 years of age, the recommended starting dose of Tekturna is 150 mg once daily. In patients whose blood pressure is not adequately controlled, the daily dose may be increased to 300 mg once daily. Doses above 300 mg did not give an increased blood pressure response but resulted in an increased rate of diarrhea. The antihypertensive effect of a given dosage is substantially attained (85% to 90%) by 2 weeks.

2.2 Relationship to Meals

Patients should establish a routine pattern for taking Tekturna with regard to meals. High-fat meals decrease absorption substantially [see Clinical Pharmacology (12.3)].

3 DOSAGE FORMS AND STRENGTHS

150 mg light pink biconvex round tablet, imprinted NVR/IL (Side 1/Side 2).

300 mg light red biconvex ovaloid round tablet, imprinted NVR/IU (Side 1/Side 2).

4 CONTRAINDICATIONS

Do not use Tekturna with ARBs or ACEIs in patients with diabetes [see Warnings and Precautions (5.2) and Clinical Studies (14.3)].

Tekturna is contraindicated in patients with known hypersensitivity to any of the components [see Warnings and Precautions (5.3)].

Tekturna is contraindicated in pediatric patients less than 2 years of age because of the risk of high aliskiren exposures identified in juvenile animals due to immaturity of transporters and metabolic enzymes [see Use in Specific Populations (8.4)].

5 WARNINGS AND PRECAUTIONS

5.1 Fetal Toxicity

Use of drugs that act on the renin-angiotensin system during the second and third trimesters of pregnancy reduces fetal renal function and increases fetal and neonatal morbidity and death. Resulting oligohydramnios can be associated with fetal lung hypoplasia and skeletal deformations. Potential neonatal adverse effects include skull hypoplasia, anuria, hypotension, renal failure, and death. When pregnancy is detected, discontinue Tekturna as soon as possible [see Use in Specific Populations (8.1)].

5.2 Renal Impairment/Hyperkalemia/Hypotension when Tekturna is Given in Combination with ARBs or ACEIs

Tekturna is contraindicated in patients with diabetes who are receiving ARBs or ACEIs because of the increased risk of renal impairment, hyperkalemia, and hypotension. In general, avoid combined use of Tekturna with ACE inhibitors or ARBs, particularly in patients with creatinine clearance (CrCl) less than 60 mL/min [see Contraindications (4), Drug Interactions (7) and Clinical Studies (14.3)] .

5.3 Anaphylactic Reactions and Head and Neck Angioedema

Hypersensitivity reactions such as anaphylactic reactions and angioedema of the face, extremities, lips, tongue, glottis and/or larynx have been reported in patients treated with Tekturna and has necessitated hospitalization and intubation. This may occur at any time during treatment and has occurred in patients with and without a history of angioedema with ACEIs or angiotensin receptor antagonists. Anaphylactic reactions have been reported from postmarketing experience with unknown frequency. If angioedema involves the throat, tongue, glottis or larynx, or if the patient has a history of upper respiratory surgery, airway obstruction may occur and be fatal. Patients who experience these effects, even without respiratory distress, require prolonged observation and appropriate monitoring measures since treatment with antihistamines and corticosteroids may not be sufficient to prevent respiratory involvement. Prompt administration of subcutaneous epinephrine solution 1:1000 (0.3 mL to 0.5 mL) and measures to ensure a patent airway may be necessary.

Discontinue Tekturna immediately in patients who develop anaphylactic reactions or angioedema, and do not readminister [see Dosage and Administration (2.1) and Contraindications (4)].

5.4 Hypotension

Symptomatic hypotension may occur after initiation of treatment with Tekturna in patients with marked volume depletion, patients with salt depletion, or with combined use of Tekturna and other agents acting on the renin-angiotensin-aldosterone system (RAAS). The volume or salt depletion should be corrected prior to administration of Tekturna, or the treatment should start under close medical supervision.

A transient hypotensive response is not a contraindication to further treatment, which usually can be continued without difficulty once the blood pressure has stabilized.

5.5 Impaired Renal Function

Monitor renal function periodically in patients treated with Tekturna. Changes in renal function, including acute renal failure, can be caused by drugs that affect the RAAS. Patients whose renal function may depend in part on the activity of the RAAS (e.g., patients with renal artery stenosis, severe heart failure, post-myocardial infarction or volume depletion) or patients receiving ARB, ACEI or nonsteroidal anti-inflammatory drug (NSAID), including selective Cyclooxygenase-2 inhibitors (COX-2 inhibitors), therapy may be at particular risk for developing acute renal failure on Tekturna [see Warnings and Precautions (5.2), Drug Interactions (7), Use in Specific Populations (8.6), and Clinical Studies (14.3)] .

Consider withholding or discontinuing therapy in patients who develop a clinically significant decrease in renal function.

5.6 Hyperkalemia

Monitor serum potassium periodically in patients receiving Tekturna. Drugs that affect the RAAS can cause hyperkalemia. Risk factors for the development of hyperkalemia include renal insufficiency, diabetes, combination use with ARBs or ACEIs [see Contraindications (4), Warnings and Precautions (5.2), and Clinical Studies (14.3)] , NSAIDs, or potassium supplements or potassium sparing diuretics.

5.7 Cyclosporine or Itraconazole

When Tekturna was given with cyclosporine or itraconazole, the blood concentrations of aliskiren were significantly increased. Avoid concomitant use of Tekturna with cyclosporine or itraconazole [see Drug Interactions (7)] .

7 DRUG INTERACTIONS

Cyclosporine: Avoid coadministration of cyclosporine with aliskiren [see Warnings and Precautions (5.7) and Clinical Pharmacology (12.3)] .

Itraconazole: Avoid coadministration of itraconazole with aliskiren [see Warnings and Precautions (5.7) and Clinical Pharmacology (12.3)].

Nonsteroidal Anti-Inflammatory Drugs (NSAIDs) including selective Cyclooxygenase-2 inhibitors (COX-2 inhibitors): In patients who are elderly, volume-depleted (including those on diuretic therapy), or with compromised renal function, coadministration of NSAIDs, including selective COX-2 inhibitors with agents that affect the RAAS, including aliskiren, may result in deterioration of renal function, including possible acute renal failure. These effects are usually reversible. Monitor renal function periodically in patients receiving aliskiren and NSAID therapy.

The antihypertensive effect of aliskiren may be attenuated by NSAIDs.

Dual Blockade of the Renin-Angiotensin-Aldosterone System (RAAS): The concomitant use of aliskiren with other agents acting on the RAAS such as ACEIs or ARBs is associated with an increased risk of hypotension, hyperkalemia, and changes in renal function (including acute renal failure) compared to monotherapy. Most patients receiving the combination of two drugs that inhibit the renin-angiotensin system do not obtain any additional benefit compared to monotherapy. In general, avoid combined use of aliskiren with ACE inhibitors or ARBs, particularly in patients with CrCl less than 60 mL/min. Monitor blood pressure, renal function, and electrolytes in patients taking aliskiren and other agents that affect the RAAS [see Warnings and Precautions (5.4, 5.5, 5.6)].

The concomitant use of aliskiren with an ARB or an ACEI in diabetic patients is contraindicated [see Contraindications (4)].

Furosemide: Oral coadministration of aliskiren and furosemide reduced exposure to furosemide. Monitor diuretic effects when furosemide is coadministered with aliskiren.

6 ADVERSE REACTIONS

Most common adverse reaction: diarrhea (incidence 2.3%) (6.1)

To report SUSPECTED ADVERSE REACTIONS, contact LXO US Inc. at 1-844-800-8007 or FDA at 1-800-FDA-1088 or www.fda.gov/medwatch.

6.1 Clinical Trials Experience

The following serious adverse reactions are discussed in greater detail in other sections of the label:

- Fetal Toxicity [see Warnings and Precautions (5.1)]
- Anaphylactic Reactions and Head and Neck Angioedema [see Warnings and Precautions (5.3)]
- Hypotension [see Warnings and Precautions (5.4)]

Because clinical trials are conducted under widely varying conditions, adverse reaction rates observed in the clinical trials of a drug cannot be directly compared to rates in clinical trials of another drug and may not reflect the rates observed in practice.

Adult Hypertension

Data described below reflect the evaluation of the safety of Tekturna in more than 6,460 patients, including over 1,740 treated for longer than 6 months, and more than 1,250 patients for longer than 1 year. In placebo-controlled clinical trials, discontinuation of therapy due to a clinical adverse event, including uncontrolled hypertension, occurred in 2.2% of patients treated with Tekturna versus 3.5% of patients given placebo. These data do not include information from the ALTITUDE study which evaluated the use of aliskiren in combination with ARBs or ACEIs [see Contraindications (4), Warnings and Precautions (5.2), and Clinical Studies (14.3)].

Angioedema: Two cases of angioedema with respiratory symptoms were reported with Tekturna use in the clinical studies. Two other cases of periorbital edema without respiratory symptoms were reported as possible angioedema and resulted in discontinuation. The rate of these angioedema cases in the completed studies was 0.06%.

In addition, 26 other cases of edema involving the face, hands, or whole body were reported with Tekturna use including 4 leading to discontinuation.

In the placebo-controlled studies, however, the incidence of edema involving the face, hands, or whole body was 0.4% with Tekturna compared with 0.5% with placebo. In a long-term active-control study with Tekturna and hydrochlorothiazide (HCTZ) arms, the incidence of edema involving the face, hand or whole body was 0.4% in both treatment arms [see Warnings and Precautions (5.2)].

Gastrointestinal: Tekturna produces dose-related gastrointestinal (GI) adverse reactions. Diarrhea was reported by 2.3% of patients at 300 mg, compared to 1.2% in placebo patients. In women and the elderly (age 65 years and older) increases in diarrhea rates were evident starting at a dose of 150 mg daily, with rates for these subgroups at 150 mg comparable to those seen at 300 mg for men or younger patients (all rates about 2.0% to 2.3%). Other GI symptoms included abdominal pain, dyspepsia, and gastroesophageal reflux, although increased rates for abdominal pain and dyspepsia were distinguished from placebo only at 600 mg daily. Diarrhea and other GI symptoms were typically mild and rarely led to discontinuation.

Cough: Tekturna was associated with a slight increase in cough in the placebo-controlled studies (1.1% for any Tekturna use versus 0.6% for placebo). In active-controlled trials with ACE inhibitor (ramipril, lisinopril) arms, the rates of cough for the Tekturna arms were about one-third to one-half the rates in the ACE inhibitor arms.

Seizures: Single episodes of tonic-clonic seizures with loss of consciousness were reported in 2 patients treated with Tekturna in the clinical trials. One of these patients did have predisposing causes for seizures and had a negative electroencephalogram (EEG) and cerebral imaging following the seizures (for the other patient EEG and imaging results were not reported). Tekturna was discontinued and there was no rechallenge.

Other adverse effects with increased rates for Tekturna compared to placebo included rash (1% versus 0.3%), elevated uric acid (0.4% versus 0.1%), gout (0.2% versus 0.1%) and renal stones (0.2% versus 0%).

Aliskiren's effect on ECG intervals was studied in a randomized, double-blind, placebo and active-controlled (moxifloxacin), 7-day repeat dosing study with Holter-monitoring and 12 lead ECGs throughout the interdosing interval. No effect of aliskiren on QT interval was seen.

Pediatric Hypertension

Aliskiren has been evaluated for safety in 267 pediatric hypertensive patients 6 to 17 years of age; including 208 patients treated for 52 weeks [see Clinical Studies (14.4)] . These studies did not reveal any unanticipated adverse reactions. Adverse reactions in pediatric patients 6 years of age and older are expected to be similar to those seen in adults.

Clinical Laboratory Findings

In controlled clinical trials, clinically relevant changes in standard laboratory parameters were rarely associated with the administration of Tekturna in patients with hypertension not concomitantly treated with an ARB or ACEI. In multiple- dose studies in hypertensive patients, Tekturna had no clinically important effects on total cholesterol, HDL, fasting triglycerides, or fasting glucose.

Blood Urea Nitrogen, Creatinine: In patients with hypertension not concomitantly treated with an ARB or ACEI, minor increases in blood urea nitrogen (BUN) or serum creatinine were observed in less than 7% of patients treated with Tekturna alone versus 6% on placebo [see Warnings and Precautions (5.2)] .

Hemoglobin and Hematocrit: Small decreases in hemoglobin and hematocrit (mean decreases of approximately 0.08 g/dL and 0.16 volume percent, respectively, for all aliskiren monotherapy) were observed. The decreases were dose-related and were 0.24 g/dL and 0.79 volume percent for 600 mg daily. This effect is also seen with other agents acting on the renin angiotensin system, such as angiotensin inhibitors and ARBs, and may be mediated by reduction of angiotensin II which stimulates erythropoietin production via the AT1 receptor. These decreases led to slight increases in rates of anemia with aliskiren compared to placebo were observed (0.1% for any aliskiren use, 0.3% for aliskiren 600 mg daily, versus 0% for placebo). No patients discontinued therapy due to anemia.

Serum Potassium: In patients with hypertension not concomitantly treated with an ARB or ACEI, increases in serum potassium greater than 5.5 mEq/L were infrequent (0.9% compared to 0.6% with placebo) [see Contraindications (4) and Warnings and Precautions (5.6)] .

Serum Uric Acid: Aliskiren monotherapy produced small median increases in serum uric acid levels (about 6 micromol/L) while HCTZ produced larger increases (about 30 micromol/L). The combination of aliskiren with HCTZ appears to be additive (about 40 micromol/L increase). The increases in uric acid appear to lead to slight increases in uric acid-related AEs: elevated uric acid (0.4% versus 0.1%), gout (0.2% versus. 0.1%), and renal stones (0.2% versus 0%).

Creatine Kinase: Increases in creatine kinase of greater than 300% were recorded in about 1% of aliskiren monotherapy patients versus 0.5% of placebo patients. Five cases of creatine kinase rises, 3 leading to discontinuation and 1 diagnosed as subclinical rhabdomyolysis, and another as myositis, were reported as adverse events with aliskiren use in the clinical trials. No cases were associated with renal dysfunction.

6.2 Postmarketing Experience

The following adverse reactions have been reported in aliskiren postmarketing experience. Because these reactions are reported voluntarily from a population of uncertain size, it is not always possible to estimate their frequency or establish a causal relationship to drug exposure.

Hypersensitivity: anaphylactic reactions and angioedema requiring airway management and hospitalization

Urticaria

Peripheral edema

Hepatic enzyme increase with clinical symptoms of hepatic dysfunction

Severe cutaneous adverse reactions, including Stevens-Johnson syndrome and toxic epidermal necrolysis

Pruritus

Erythema

Hyponatremia

Nausea, Vomiting

8 USE IN SPECIFIC POPULATIONS

8.1 Pregnancy

Risk Summary

Tekturna can cause fetal harm when administered to a pregnant woman. Use of drugs that act on the renin-angiotensin system during the second and third trimesters of pregnancy reduces fetal renal function and increases fetal and neonatal morbidity and death [see Clinical Considerations] . Most epidemiologic studies examining fetal abnormalities after exposure to antihypertensive use in the first trimester have not distinguished drugs affecting the renin-angiotensin system from other antihypertensive agents. When pregnancy is detected, discontinue Tekturna as soon as possible.

The estimated background risk of major birth defects and miscarriage for the indicated population is unknown. All pregnancies have a background risk of birth defect, loss, or other adverse outcomes. In the U.S. general population, the estimated background risk of major malformations and miscarriage in clinically recognized pregnancies is 2-4%, and 15-20%, respectively.

Clinical Considerations

Disease-Associated Maternal and/or Embryo/Fetal Risk

Hypertension in pregnancy increases the maternal risk for pre-eclampsia, gestational diabetes, premature delivery, and delivery complications (e.g., need for cesarean section, and post-partum hemorrhage).

Hypertension increases the fetal risk for intrauterine growth restriction and intrauterine death. Pregnant women with hypertension should be carefully monitored and managed accordingly.

Fetal/Neonatal Adverse Reactions

Use of drugs that act on the renin-angiotensin system in the second and third trimesters of pregnancy can result in the following: reduced fetal renal function leading to anuria and renal failure, oligohydramnios, fetal lung hypoplasia and skeletal deformations, including skull hypoplasia, hypotension, and death. In the unusual case that there is no appropriate alternative to therapy with drugs affecting the renin-angiotensin system for a particular patient, apprise the mother of the potential risk to the fetus.

In patients taking Tekturna during pregnancy, perform serial ultrasound examinations to assess the intra- amniotic environment. Fetal testing may be appropriate, based on the week of gestation. Patients and physicians should be aware, however, that oligohydramnios may not appear until after the fetus has sustained irreversible injury. Closely observe infants with histories of in utero exposure to Tekturna for hypotension, oliguria, and hyperkalemia. If oliguria or hypotension occur in neonates with a history of in utero exposure to aliskiren, support blood pressure and renal perfusion. Exchange transfusions or dialysis may be required as a means of reversing hypotension and substituting for disordered renal function.

Data

Animal Data

In developmental toxicity studies, pregnant rats and rabbits received oral aliskiren hemifumarate during organogenesis at doses up to 20 and 7 times the maximum recommended human dose (MRHD) based on body surface area (mg/m^2), respectively, in rats and rabbits. (Actual animal doses were up to 600 mg/kg/day in rats and up to 100 mg/kg/day in rabbits.) No teratogenicity was observed; however, fetal birth weight was decreased in rabbits at doses 3.2 times the MRHD based on body surface area (mg/m^2). Aliskiren was present in placentas, amniotic fluid and fetuses of pregnant rabbits.

8.2 Lactation

Risk Summary

There is no information regarding the presence of aliskiren in human milk, the effects on the breastfed infant, or the effects on milk production. Because of the potential for serious adverse reactions, including hypotension, hyperkalemia and renal impairment in nursing infants, advise a nursing woman that breastfeeding is not recommended during treatment with Tekturna.

8.4 Pediatric Use

Tekturna is contraindicated in patients less than 2 years of age [see Contraindications (4)].

Tekturna is indicated for treatment of hypertension in pediatric patients 6 years of age and older weighing 50 kg or more. The safety and effectiveness of aliskiren have been established in pediatric patients 6 years of age and older weighing 20 kg or more, but Tekturna is not approved in patients 6 years of age and older weighing 20 kg to less than 50 kg because of the lack of an appropriate dosage form. Use of Tekturna in pediatric patients 6 years and older is supported by evidence from a pharmacokinetic trial and two randomized, double-blind clinical trials in pediatric patients with hypertension 6 years to 17 years of age weighing 20 kg or more [see Clinical Pharmacology (12.3), Clinical Studies (14.4) ].

The safety and effectiveness of Tekturna have not been established in pediatric patients younger than 6 years of age and patients less than 20 kg. Avoid use in patients 2 years to less than 6 years and patients weighing less than 20 kg due to the limited information about aliskiren metabolism and exposures in this age group. No data are available in pediatric patients weighing less than 20 kg or in pediatric patients with a glomerular filtration rate <30 mL/min/1.73 m^2.

Juvenile Animal Toxicity Data

Toxicology studies in juvenile animals the approximate human age equivalent of children less than 2 years of age identified 85- to 385-fold increased systemic exposure to aliskiren compared to adult rats. The increased aliskiren exposure in juvenile rats was attributed to immaturity in aliskiren drug transporters and metabolizing enzymes. Increased aliskiren exposures were associated with premature deaths. Although a definitive pathology-based cause of death could not be ascertained, the premature deaths were attributed to the immaturity in aliskiren metabolism. The nonclinical findings suggest a distinct age-dependent relationship between dose and exposure.

Neonates with a history of in utero exposure to Tekturna

If oliguria or hypotension occurs, direct attention toward support of blood pressure and renal perfusion. Exchange transfusions or dialysis may be required as a means of reversing hypotension and/or substituting for disordered renal function.

8.5 Geriatric Use

Of the total number of patients receiving aliskiren in clinical studies, 1,275 (19%) were 65 years or older and 231 (3.4%) were 75 years or older. No overall differences in safety or effectiveness were observed between these subjects and younger subjects. Other reported clinical experience has not identified differences in responses between the elderly and younger patients, but greater sensitivity of some older individuals cannot be ruled out.

8.6 Renal Impairment

Safety and effectiveness of Tekturna in patients with severe renal impairment [creatinine clearance (CrCl) less than 30 mL/min] have not been established as these patients were excluded in efficacy trials [see Clinical Studies (14)].

10 OVERDOSAGE

Limited data are available related to overdosage in humans. The most likely manifestation of overdosage would be hypotension. If symptomatic hypotension occurs, supportive treatment should be initiated.

Aliskiren is poorly dialyzed. Therefore, hemodialysis is not adequate to treat aliskiren overexposure [see Clinical Pharmacology (12.3)] .

11 DESCRIPTION

Tekturna contains aliskiren hemifumarate, adirect renin inhibitor. Aliskiren hemifumarate is chemically described as (2S,4S,5S,7S)-N-(2-carbamoyl-2-methylpropyl)-5-amino-4-hydroxy- 2,7-diisopropyl-8-[4-methoxy-3-(3-methoxypropoxy)phenyl]-octanamide hemifumarate and its structural formula is:

Molecular formula: C30H53N3O6 • 0.5 C4H4O4

Aliskiren hemifumarate is a white to slightly yellowish crystalline powder with a molecular weight of 609.8 (free base- 551.8). It is soluble in phosphate buffer, n-octanol, and highly soluble in water.

Tekturna is available as film-coated tablets, which contains 165.75 mg or 331.5 mg aliskiren hemifumerate (equivalent to 150 mg or 300 mg aliskiren) and the following excipients: crospovidone; magnesium stearate; microcrystalline cellulose; povidone; silica, colloidal anhydrous; hypromellose; macrogol; talc; iron oxide, black (E 172); iron oxide, red (E 172); titanium dioxide (E 171).

12 CLINICAL PHARMACOLOGY

12.1 Mechanism of Action

Renin is secreted by the kidney in response to decreases in blood volume and renal perfusion. Renin cleaves angiotensinogen to form the inactive decapeptide angiotensin I (Ang I). Ang I is converted to the active octapeptide angiotensin II (Ang II) by ACE and non-ACE pathways. Ang II is a powerful vasoconstrictor and leads to the release of catecholamines from the adrenal medulla and prejunctional nerve endings. It also promotes aldosterone secretion and sodium reabsorption. Together, these effects increase blood pressure. Ang II also inhibits renin release, thus providing a negative feedback to the system. This cycle, from renin through angiotensin to aldosterone and its associated negative feedback loop, is known as the renin-angiotensin-aldosterone system (RAAS). Aliskiren is a direct renin inhibitor, decreasing plasma renin activity (PRA) and inhibiting the conversion of angiotensinogen to Ang I. Whether aliskiren affects other RAAS components, e.g., ACE or non-ACE pathways, is not known.

All agents that inhibit the RAAS, including renin inhibitors, suppress the negative feedback loop, leading to a compensatory rise in plasma renin concentration. When this rise occurs during treatment with ACEIs and ARBs, the result is increased levels of PRA. During treatment with aliskiren, however, the effect of increased renin levels is blocked so that PRA, Ang I and Ang II are all reduced, whether aliskiren is used as monotherapy or in combination with other antihypertensive agents.

12.2 Pharmacodynamics

In placebo-controlled clinical trials, PRA was decreased in a range of 50% to 80%. This reduction in PRA was not dose- related and did not correlate with blood pressure reductions. The clinical implications of the differences in effect on PRA are not known.

12.3 Pharmacokinetics

Aliskiren is poorly absorbed (bioavailability about 2.5%) with an approximate accumulation half-life of 24 hours. Steady state blood levels are reached in about 7 to 8 days.

Absorption and Distribution

Following oral administration, peak plasma concentrations of aliskiren are reached within 1 to 3 hours. When taken with a high-fat meal, mean AUC and Cmax of aliskiren are decreased by 71% and 85% respectively. In the clinical trials of aliskiren, it was administered without requiring a fixed relation of administration to meals.

Metabolism and Elimination

About one-fourth of the absorbed dose appears in the urine as parent drug. How much of the absorbed dose is metabolized is unknown. Based on the in vitro studies, the major enzyme responsible for aliskiren metabolism appears to be CYP3A4. Aliskiren does not inhibit the CYP450 isoenzymes (CYP 1A2, 2C8, 2C9, 2C19, 2D6, 2E1, and 3A) or induce CYP3A4.

Transporters: Pgp (MDR1/Mdr1a/1b) was found to be the major efflux system involved in intestinal absorption and elimination via biliary excretion of aliskiren in preclinical studies. The potential for drug interactions at the Pgp site will likely depend on the degree of inhibition of this transporter.

Drug Interactions

The effect of coadministered drugs on the pharmacokinetics of aliskiren and vice versa, were studied in several single- and multiple-dose studies. Pharmacokinetic measures indicating the magnitude of these interactions are presented in Figure 1(impact of coadministered drugs on aliskiren) and Figure 2(impact of aliskiren on coadministered drugs).

Figure 1: The Impact of Coadministered Drugs on the Pharmacokinetics of Aliskiren

*Ketoconazole: A 400 mg once daily dose was not studied, but would be expected to increase aliskiren blood levels further.

**Ramipril, valsartan, irbesartan: In general, avoid combined use of aliskiren with ACE inhibitors or ARBs, particularly in patients with CrCl less than 60 mL/min [see Drug Interactions (7)].

Warfarin: There was no clinically significant effect of a single dose of warfarin 25 mg on the pharmacokinetics of aliskiren.

Figure 2: The Impact of Aliskiren on the Pharmacokinetics of Coadministered Drugs

*Furosemide: Patients receiving furosemide could find its effects diminished after starting aliskiren. In patients with heart failure, coadministration of aliskiren (300 mg/day) reduced plasma AUC and Cmaxof oral furosemide (60 mg/day) by 17% and 27%, respectively, and reduced 24-hour urinary furosemide excretion by 29%. This change in exposure did not result in statistically significant difference in total urine volume and urinary sodium excretion over 24 hours. However, a transient decrease in urinary sodium excretion and urine volume effects up to 12 hours were observed when furosemide was coadministered with aliskiren 300 mg/day.

**Ramipril, valsartan: In general, avoid combined use of aliskiren with ACE inhibitors or ARBs, particularly in patients with CrCl less than 60 mL/min [see Drug Interactions (7)].

Specific Populations

Renally Impaired Patients: Aliskiren was evaluated in adult patients with varying degrees of renal insufficiency. The rate and extent of exposure (AUC and Cmax) of aliskiren in subjects with renal impairment did not show a consistent correlation with the severity of renal impairment. Adjustment of the starting dose is not required in these patients [see Warnings and Precautions (5.2)] .

The pharmacokinetics of aliskiren following administration of a single oral dose of 300 mg was evaluated in adult patients with End Stage Renal Disease (ESRD) undergoing hemodialysis. When compared to matched healthy subjects, changes in the rate and extent of aliskiren exposure (Cmax and AUC) in ESRD patients undergoing hemodialysis were not clinically significant.

Timing of hemodialysis did not significantly alter the pharmacokinetics of aliskiren in ESRD patients. Therefore, no dose adjustment is warranted in ESRD patients receiving hemodialysis.

Hepatically Impaired Patients: The pharmacokinetics of aliskiren were not significantly affected in patients with mild to severe liver disease. Consequently, adjustment of the starting dose is not required in these patients.

Pediatric Patients:

The pharmacokinetics of aliskiren were evaluated in an 8-day pharmacokinetic study in 39 pediatric patients with hypertension 6 years to 17 years of age. Aliskiren was given as daily doses of 2 mg/kg (0.67 times the lowest approved recommended dosage in a 50 kg pediatric patient) or 6 mg/kg (the highest recommended approved dosage in a 50 kg pediatric patient), administered as mini-tablets (3.125 mg oral pellets). The pharmacokinetic parameters of aliskiren were similar to those in adults, and the results of this study do not suggest that age or gender have any significant effect on aliskiren systemic exposure in patients 6 years to 17 years of age. Exposure decreased with increase in body weight.

In an 8-week randomized double blind study with aliskiren monotherapy in 267 pediatric patients with hypertension 6 years to 17 years of age [see Clinical Studies (14.4)] , fasting trough aliskiren concentrations at Day 28 demonstrated similar drug trough exposure levels to those observed in other trials using similar aliskiren doses in both adults and pediatric patients.

Geriatric Patients: Exposure (measured by AUC) is increased in elderly patients 65 years and older. Adjustment of the starting dose is not required in these patients.

Racial or Ethnic Groups: The pharmacokinetic differences between blacks, Caucasians, and Japanese are minimal.

13 NONCLINICAL TOXICOLOGY

13.1 Carcinogenesis, Mutagenesis, Impairment of Fertility

Carcinogenic potential was assessed in a 2-year rat study and a 6-month transgenic (rasH2) mouse study with aliskiren hemifumarate at oral doses of up to 1500 mg aliskiren/kg/day. Although there were no statistically significant increases in tumor incidence associated with exposure to aliskiren, mucosal epithelial hyperplasia (with or without erosion/ulceration) was observed in the lower gastrointestinal tract at doses of greater than or equal to 750 mg/kg/day in both species, with a colonic adenoma identified in 1 rat and a cecal adenocarcinoma identified in another, rare tumors in the strain of rat studied. On a systemic exposure (AUC0-24hr) basis, 1500 mg/kg/day in the rat is about 4 times and in the mouse about 1.5 times the maximum recommended human dose (MRHD) (300 mg aliskiren/day). Mucosal hyperplasia in the cecum or colon of rats was also observed at doses of 250 mg/kg/day (the lowest tested dose) as well as at higher doses in 4- and 13- week studies.

Aliskiren hemifumarate was devoid of genotoxic potential in the Ames reverse mutation assay with S. typhimurium and

E. coli, the in vitro Chinese hamster ovary cell chromosomal aberration assay, the in vitro Chinese hamster V79 cell gene mutation test and the in vivo mouse bone marrow micronucleus assay.

Fertility of male and female rats was unaffected at doses of up to 250 mg aliskiren/kg/day (8 times the MRHD of 300 mg Tekturna/60 kg on a mg/m^2 basis.)

13.2 Animal Toxicology and/or Pharmacology

Reproductive Toxicology Studies: Reproductive toxicity studies of aliskiren hemifumarate did not reveal any evidence of teratogenicity at oral doses up to 600 mg aliskiren/kg/day (20 times the MRHD of 300 mg/day on a mg/m^2 basis) in pregnant rats or up to 100 mg aliskiren/kg/day (7 times the MRHD on a mg/m^2 basis) in pregnant rabbits. Fetal birth weight was adversely affected in rabbits at 50 mg/kg/day (3.2 times the MRHD on a mg/m^2 basis). Aliskiren was present in placenta, amniotic fluid and fetuses of pregnant rabbits.

14 CLINICAL STUDIES

14.1 Aliskiren Monotherapy

The antihypertensive effects of Tekturna have been demonstrated in 6 randomized, double-blind, placebo-controlled 8- week clinical trials in patients with mild-to-moderate hypertension. The placebo response and placebo-subtracted changes from baseline in seated trough cuff blood pressure are shown in Table 2.

Table 2: Reductions in Seated Trough Cuff Blood Pressure (mmHg systolic/diastolic) in the Placebo-Controlled Studies
 |  | Aliskiren daily dose, mg
Study | Placebo mean change | 75 | 150 | 300 | 600
Study | Placebo mean change | Placebo-subtracted | Placebo-subtracted | Placebo-subtracted | Placebo-subtracted
1 | 2.9/3.3 | 5.7/4* | 5.9/4.5* | 11.2/7.5* | --
2 | 5.3/6.3 | -- | 6.1/2.9* | 10.5/5.4* | 10.4/5.2*
3 | 10/8.6 | 2.2/1.7 | 2.1/1.7 | 5.1/3.7* | --
4 | 7.5/6.9 | 1.9/1.8 | 4.8/2* | 8.3/3.3* | --
5 | 3.8/4.9 | -- | 9.3/5.4* | 10.9/6.2* | 12.1/7.6*
6 | 4.6/4.1 | -- | -- | 8.4/4.9† | --
*p value less than 0.05 versus placebo by ANCOVA with Dunnett's procedure for multiple comparisons
†p value less than 0.05 versus placebo by ANCOVA for the pairwise comparison.

The studies included approximately 2,730 patients given doses of 75 mg (0.5 times the lowest recommended dosage) to 600 mg (twice the highest recommended dosage) of aliskiren and 1,231 patients given placebo. The recommended dosage of Tekturna is either 150 or 300 mg once daily [see Dosage and Administration (2.1)]. As shown in Table 1, there is some increase in response with administered dose in all studies, with reasonable effects seen at 150mg to 300 mg, and no clear further increases at 600 mg. A substantial proportion (85% to 90%) of the blood pressure-lowering effect was observed within 2 weeks of treatment. Studies with ambulatory blood pressure monitoring showed reasonable control throughout the interdosing interval; the ratios of mean daytime to mean nighttime ambulatory BP range from 0.6 to 0.9.

Patients in the placebo-controlled trials continued open-label aliskiren for up to 1 year. A persistent blood pressure- lowering effect was demonstrated by a randomized withdrawal study (patients randomized to continue drug or placebo), which showed a statistically significant difference between patients kept on aliskiren and those randomized to placebo. With cessation of treatment, blood pressure gradually returned toward baseline levels over a period of several weeks.

There was no evidence of rebound hypertension after abrupt cessation of therapy.

Aliskiren lowered blood pressure in all demographic subgroups, although black patients tended to have smaller reduction than Caucasians and Asians, as has been seen with ACEIs and ARBs.

There are no studies of Tekturna or members of the direct renin inhibitors demonstrating reductions in cardiovascular risk in patients with hypertension.

14.2 Aliskiren in Combination with Other Antihypertensives

Hydrochlorothiazide (HCTZ)

Aliskiren 75, 150, and 300 mg (0.5 times the recommended lowest dosage, the lowest recommended dosage, and the maximum recommended dosage, respectively) and HCTZ 6.25, 12.5, and 25 mg were studied alone and in combination in an 8-week, 2,776-patient, randomized, double-blind, placebo-controlled, parallel-group, 15-arm factorial study. Blood pressure reductions with the combinations were greater than the reductions with the monotherapies as shown in Table 3.

Table 3: Placebo-Subtracted Reductions in Seated Trough Cuff Blood Pressure (mmHg systolic/diastolic) in Combination with Hydrochlorothiazide
 |  | Hydrochlorothiazide, mg
Aliskiren, mg | Placebo mean change | 0 | 6.25 | 12.5 | 25
Aliskiren, mg | Placebo mean change | Placebo- subtracted | Placebo- subtracted | Placebo- subtracted | Placebo- subtracted
0 | 7.5/6.9 | -- | 3.5/2.1 | 6.4/3.2 | 6.8/2.4
75 | -- | 1.9/1.8 | 6.8/3.8 | 8.2/4.2 | 9.8/4.5
150 | -- | 4.8/2 | 7.8/3.4 | 10.1/5 | 12/5.7
300 | -- | 8.3/3.3 | -- | 12.3/7 | 13.7/7.3

Valsartan

Aliskiren 150 mg and 300 mg and valsartan 160 mg and 320 mg were studied alone and in combination in an 8-week, 1,797-patient, randomized, double-blind, placebo-controlled, parallel-group, 4-arm, dose-escalation study. The dosages of aliskiren and valsartan were started at 150 mg and 160 mg, respectively, and increased at 4 weeks to 300 mg and 320 mg, respectively. Seated trough cuff blood pressure was measured at baseline, 4, and 8 weeks. Blood pressure reductions with the combinations were greater than the reductions with the monotherapies as shown in Table 4. In general, the combination of aliskiren and angiotensin receptor blocker should be avoided [see Contraindications (4), Warnings and Precautions (5), and Drug Interactions (7)].

Table 4: Placebo-Subtracted Reductions in Seated Trough Cuff Blood Pressure (mmHg systolic/diastolic) in Combination with Valsartan
Aliskiren, mg | Placebo mean change |  | Valsartan, mg
 |  | 0 | 160 | 320
0 | 4.6/4.1* | -- | 5.6/3.9 | 8.2/5.6
150 | -- | 5.4/2.7 | 10.0/5.7 | --
300 | -- | 8.4/4.9 | -- | 12.6/8.1
* The placebo change is 5.2/4.8 for week 4 endpoint which was used for the dose groups containing aliskiren 150 mg or valsartan 160 mg.

Amlodipine

Aliskiren 150 mg and 300 mg and amlodipine besylate 5 mg and 10 mg were studied alone and in combination in an 8- week, 1,685-patient, randomized, double-blind, placebo-controlled, multifactorial study. Treatment with aliskiren and amlodipine resulted overall in significantly greater reductions in diastolic and systolic blood pressure compared to the respective monotherapy components as shown in Table 5.

Table 5: Placebo-Subtracted Reductions in Seated Trough Cuff Blood Pressure (mmHg systolic/diastolic) in Combination with Amlodipine
Aliskiren, mg | Placebo mean change | Amlodipine, mg
Aliskiren, mg | Placebo mean change | 0 | 5 | 10
0 | 6.8/5.4 | -- | 9.0/5.6 | 14.3/8.5
150 | -- | 3.9/2.6 | 13.9/8.6 | 17.1/10.8
300 | -- | 8.6/4.9 | 15.0/9.6 | 16.4/11.1

14.3 Aliskiren in Patients with Diabetes Treated with ARB or ACEI (ALTITUDE study)

Patients with diabetes with renal disease (defined either by the presence of albuminuria or reduced GFR) were randomized to aliskiren 300 mg daily (n=4296) or placebo (n=4310). All patients were receiving background therapy with an ARB or ACEI. The primary efficacy outcome was the time to the first event of the primary composite endpoint consisting of cardiovascular death, resuscitated sudden death, nonfatal myocardial infarction, nonfatal stroke, unplanned hospitalization for heart failure, onset of end stage renal disease, renal death, and doubling of serum creatinine concentration from baseline sustained for at least 1 month. After a median follow-up of about 32 months, the trial was terminated early for lack of efficacy. Higher risk of renal impairment, hypotension and hyperkalemia was observed in aliskiren compared to placebo-treated patients, as shown in Table 6.

Table 6: Incidence of Selected Adverse Events During the Treatment Phase in ALTITUDE
 | Aliskiren N=4272 |  | Placebo N=4285
 | Serious Adverse Events* (%) | Adverse Events (%) | Serious Adverse Events* (%) | Adverse Events (%)
Renal impairment † | 5.7 | 14.5 | 4.3 | 12.4
Hypotension †† | 2.3 | 19.9 | 1.9 | 16.3
Hyperkalemia ††† | 1.0 | 38.9 | 0.5 | 28.8
†renal failure, renal failure acute, renal failure chronic, renal impairment
††dizziness, dizziness postural, hypotension, orthostatic hypotension, presyncope, syncope
††† Given the variable baseline potassium levels of patients with renal insufficiency on dual RAAS therapy, the reporting of adverse event of hyperkalemia was at the discretion of the investigator.
* A Serious Adverse Event (SAE) is defined as: an event which is fatal or life-threatening, results in persistent or significant disability/incapacity, constitutes a congenital anomaly/birth defect, requires inpatient hospitalization or prolongation of existing hospitalization, or is medically significant (i.e., defined as an event that jeopardizes the patient or may require medical or surgical intervention to prevent one of the outcomes previously listed).

The risk of stroke (3.4% aliskiren versus 2.7% placebo) and death (8.4% aliskiren versus 8.0% placebo) were also numerically higher in aliskiren treated patients.

14.4 Pediatric Hypertension

The efficacy of aliskiren was evaluated in an 8-week randomized, double-blind trial in 267 pediatric patients with hypertension 6 years to 17 years of age (Study CSPP100A2365; NCT01150357). The majority of patients (82%) had primary hypertension, 59% had a BMI ≥95th percentile, 20% had an estimated GFR between 60 and 90 mL/min/1.73m^2 and < 2% had an estimated GFR < 60 mL/min/1.73m^2. The mean age was 11.8 years and 74% of patients were Caucasian. In the initial 4-week,dose-response phase of the trial patients were randomized to weight-based low, mid and high dosing groups. At the end of this phase, patients entered a 4-week randomized withdrawal phase in which they were re-randomized in each weight category in a 1:1 ratio to continue the same dose of aliskiren or take placebo.

During the initial dose-response phase, aliskiren reduced both systolic and diastolic blood pressure in a weight-based dose-dependent manner. Sitting systolic blood pressure, the trial's primary endpoint, was reduced by 4.8, 5.6 and 8.7 mmHg from baseline in the low, medium and high dose groups, respectively. In the randomized withdrawal phase, the mean difference between the high dose group of aliskiren and placebo in the mean change in sitting systolic blood pressure was -2.7 mmHg.

Following the 8-week trial, 208 patients were enrolled in a 52-week extension trial in which patients were randomized in a 1:1 ratio (irrespective of whether they were on placebo or aliskiren at the end of the 8-week study) to receive either aliskiren or enalapril (CSPP100A2365E1; NCT01151410). The extension study included 3 dose levels based on weight; optional dose up-titrations were allowed during the study to control blood pressure.

At the end of 52 weeks, reductions in blood pressure from baseline were similar in patients receiving aliskiren (7.6/3.9 mmHg) and enalapril (7.9/4.9 mmHg).

16 HOW SUPPLIED/STORAGE AND HANDLING

Tekturna tablets are supplied as a light-pink, biconvex round tablet containing 150 mg of aliskiren, and as a light-red biconvex ovaloid tablet containing 300 mg of aliskiren. Tablets are imprinted with NVR on one side and IL, IU, on the other side of the 150 mg and 300 mg tablets, respectively.

All strengths are packaged in bottles and unit-dose blister packages (10 strips of 10 tablets) as described below in Table 7.

Table 7: Tekturna Tablets Supply
Tablet | Color | Imprint | Imprint | NDC 70839-XXX-XX
 |  | Side 1 | Side 2 | Bottle of 30 | Bottle of 90 | Blister Packages of 100
150 mg | Light-Pink | NVR | IL | 150-30 | 150-90 | 150-01
300 mg | Light-Red | NVR | IU | 300-30 | 300-90 | 300-01

Store at 20°C to 25ºC (68°F to 77ºF); excursions permitted to 15ºC to 30ºC (59 ºF to 86ºF) [See USP Controlled Room Temperature]. Protect from moisture.

Dispense blisters in original container.

17 PATIENT COUNSELING INFORMATION

Advise the patient to read the FDA-approved patient labeling (Patient Information) and Instructions for Use.

Information for Patients

Pregnancy: Advise female patients of child-bearing age about the consequences of exposure to Tekturna during pregnancy. Discuss treatment options with women planning to become pregnant. Advise patients to report pregnancies to their physicians as soon as possible.

Lactation: Advise nursing women that breastfeeding is not recommended during treatment with Tekturna [see Use in Specific Populations (8.2)].

Anaphylactic Reactions and Angioedema: Advise patients to immediately report any signs or symptoms suggesting a severe allergic reaction (difficulty breathing or swallowing, tightness of the chest, hives, general rash, swelling, itching, dizziness, vomiting, or abdominal pain) or angioedema (swelling of face, extremities, eyes, lips, tongue, difficulty in swallowing or breathing) and to take no more drug until they have consulted with the prescribing physicians.

Angioedema, including laryngeal edema, may occur at any time during treatment with Tekturna.

Symptomatic Hypotension: Advise patients that lightheadedness can occur, especially during the first days of Tekturna therapy, and that it should be reported to the prescribing physician. Advise patients that if syncope occurs, Tekturna should be discontinued until the physician has been consulted.

Caution patients that inadequate fluid intake, excessive perspiration, diarrhea, or vomiting can lead to an excessive fall in blood pressure, with the same consequences of lightheadedness and possible syncope.

Potassium Supplements: Advise patients receiving Tekturna not to use potassium supplements or salt substitutes containing potassium without consulting the prescribing physician.

Relationship to Meals: Advise patients to establish a routine pattern for taking Tekturna with regard to meals. High-fat meals decrease absorption substantially.

PATIENT INFORMATION
Tekturna® (tek-turn-a)
(aliskiren)
tablets

What is the most important information I should know about Tekturna?
Tekturna can cause harm or death to your unborn baby.

- Talk to your doctor about other ways to lower your blood pressure if you plan to become pregnant.
- If you become pregnant during treatment with Tekturna, stop taking Tekturna and tell your doctor right away.

What is Tekturna?
Tekturna is a prescription medicine used to treat high blood pressure (hypertension) in adults and children weighing 50 kg or greater who are at least 6 years of age to lower blood pressure.
It is not known if Tekturna is safe and effective in children under 6 years of age.

Do not take Tekturna if:

- you have diabetes and are taking a kind of medicine called an angiotensin receptor blocker (ARB) or angiotensin-converting enzyme inhibitor (ACEI).
- you are allergic to any of the ingredients in Tekturna. See the end of this leaflet for a complete list of the ingredients in Tekturna.

Do not give Tekturna to children less than 2 years of age.

Before taking Tekturna, tell your doctor about all of your medical conditions, including if you:

- have kidney or heart problems.
- have diabetes.
- have ever had an allergic reaction to another blood pressure medicine.
- are pregnant or plan to become pregnant. See “ What is the most important information I should know about Tekturna?”
- are breastfeeding or plan to breastfeed. It is not known if Tekturna passes into your breast milk. You should not breastfeed during treatment with Tekturna.

Tell your doctor about all the medicines you take, including prescription and over-the-counter medicines, vitamins and herbal supplements. Especially tell your doctor if you are taking:

- a kind of medicine to control blood pressure called angiotensin receptor blocker (ARB) or angiotensin-converting enzyme inhibitor (ACEI).
- water pills (also called “diuretics”).
- cyclosporine (Gengraf®, Neoral®, Sandimmune®)
- itraconazole (Onmel®, Sporanox®).
- potassium-containing medicines, potassium supplements, or salt substitutes containing potassium.
- nonsteroidal anti-inflammatory drugs (NSAIDs).

Ask your doctor if you are not sure if you are taking one of the medicines listed above.
Know the medicines you take. Keep a list of them to show your doctor or pharmacist when you get a new medicine. Your doctor or pharmacist will know what medicines are safe to take together.

How should I take Tekturna tablets?

- Take Tekturna exactly as your doctor tells you to take it.
- Take Tekturna 1 time a day, about the same time each day.
- Your doctor may change your dose if needed.

What are possible side effects of Tekturna?
Tekturna may cause serious side effects, including:

- See “ What is the most important information I should know about Tekturna?”
- Serious allergic reactions that can be life threatening. Stop taking Tekturna and get emergency medical help right away and if you get any of these symptoms of a serious reactions during treatment with Tekturna:

- trouble breathing or swallowing
- chest tightness
- aised bumps (hives)
- rash
- swelling of the face, lips, tongue,
- throat, arms, legs or the whole body

- itching
- dizziness
- vomiting
- stomach (abdomen) pain

- Low blood pressure (hypotension). Your blood pressure may get too low if you also take water pills, are on a low-salt diet, sweat more than normal, receive dialysis treatments, have heart problems, or have vomiting or diarrhea. Lie down if you feel faint or dizzy and call your doctor right away.
- Kidney problems, including kidney failure. Tell your doctor if you urinate less.
- Increased potassium blood levels (hyperkalemia). Your doctor will check your potassium blood level during treatment with Tekturna.

The most common side effect of Tekturna is diarrhea.
These are not all of the possible side effects of Tekturna.
Call your doctor for medical advice about side effects. You may report side effects to FDA at 1-800-FDA-1088.

How should I store Tekturna tablets?

- Store Tekturna at room temperature between 68°F to 77°F (20°C to 25°C).
- Keep Tekturna in the original container it comes in. Do not remove the desiccant (drying agent) from the bottle.
- Protect Tekturna from moisture.

Keep Tekturna and all medicines out of the reach of children.

General information about the safe and effective use of Tekturna.
Medicines are sometimes prescribed for purpose other than those listed in the Patient Information leaflet. Do not take Tekturna for a condition for which it was not prescribed. Do not give Tekturna to other people, even if they have the same symptoms that you have. It may harm them. You can ask your doctor or pharmacist for information that is written for healthcare professionals.

What is high blood pressure (hypertension)?
Blood pressure is the force in your blood vessels when your heart beats and when your heart rests. You have high blood pressure when the force is too great. High blood pressure makes the heart work harder to pump blood through the body and causes damage to the blood vessels. Tekturna can help your blood vessels relax so your blood pressure is lower. Medicines that lower your blood pressure lower your chance of having a stroke or heart attack.

What are the ingredients in Tekturna?
Tekturna is available as film-coated tablets, which contains 165.75 mg or 331.5 mg aliskiren hemifumerate (equivalent to 150 mg or 300 mg aliskiren).
Active ingredient: aliskiren hemifumarate
Tekturna tablets inactive ingredients: crospovidone, magnesium stearate, microcrystalline cellulose, povidone, silica, colloidal anhydrous, hypromellose, macrogol, talc, iron oxide, black (E172), iron oxide, red (E172), and titanium dioxide (E171).
Distributed by: LXO US Inc., 1690 Sumneytown Pike, Suite 250 Lansdale, PA 19446
For more information about Tekturna, go to www.Tekturna.com, or call 1-844-800-8007.

This Patient Information has been approved by the U.S. Food and Drug Administration

PACKAGE LABEL

Principal Display Panel - Package Label – 300 mg Bottle Label

NDC 70839-300-30 30 tablets

Tekturna®

(aliskiren)

Tablets

Rx only 300 mg

LXO

PACKAGE LABEL

Principal Display Panel - Package Label – 150 mg Bottle Label

NDC 70839-150-30 30 tablets

Tekturna®

(aliskiren)

Tablets

Rx only 150 mg

LXO